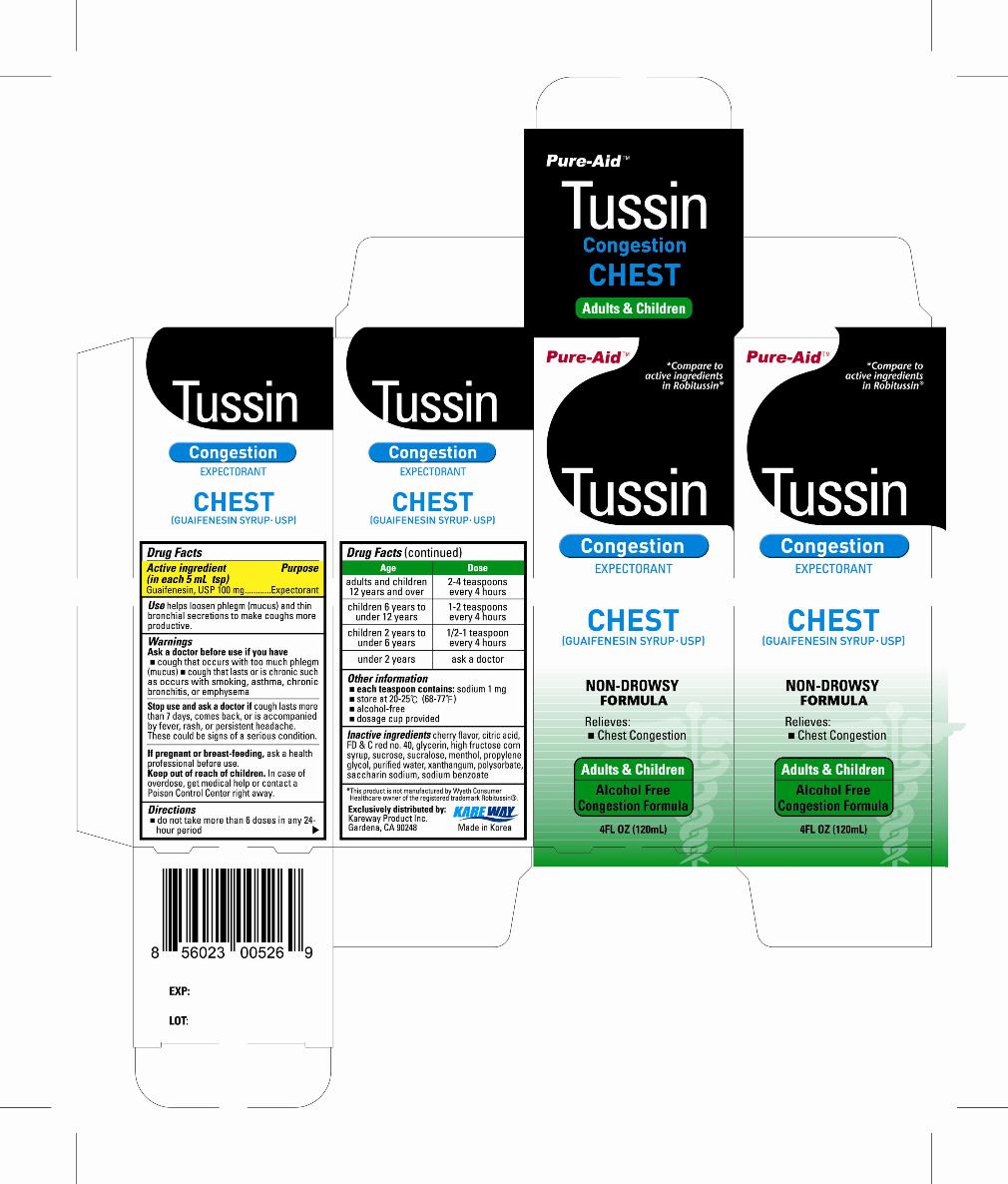 DRUG LABEL: Tussin Chest
NDC: 67510-0526 | Form: LIQUID
Manufacturer: Kareway Product, Inc.
Category: otc | Type: HUMAN OTC DRUG LABEL
Date: 20110829

ACTIVE INGREDIENTS: GUAIFENESIN 100 mg/5 mL
INACTIVE INGREDIENTS: CITRIC ACID MONOHYDRATE; FD&C RED NO. 40; GLYCERIN; HIGH FRUCTOSE CORN SYRUP; SUCROSE; SUCRALOSE; MENTHOL; PROPYLENE GLYCOL; WATER; XANTHAN GUM; POLYSORBATE 80; SACCHARIN SODIUM; SODIUM BENZOATE

Drug Facts

Active ingredients

(in each 5mL tsp)

Guaifenesin, USP 100mg

Purpose

Expectorant

Uses

helps loosen phlegm (mucus) and thin bronchial secretions to make coughs more productive.

Warnings

Ask a doctor before use if you have

- cough that occurs with too much phlegm (mucus)
- cough that lasts or is chronic such as occurs with smoking, asthma, chronic bronchitis, or emphysema

Stop use and ask a doctor if,

cough lasts more than 7 days, comes back, or is accompanied by fever, rash, or persistent headache. These could be signs of a serious condition.

If pregnant or breast-feeding,

ask a health professional before use.

Keep out of reach of children.

In case of overdose, get medical help or contact a Poison Control Center right away.

Directions

- do not take more than 6 doses in any 24-hour period

Age | Dose
adults and children 12 years and over | 2-4 tsp every 4 hours
children 6 years to under 12 years | 1-2 tsp every 4 hours
children 2 years to under 6 years | 1/2-1 tsp every 4 hours
under 2 years | ask a doctor

Other information

- each teaspoon contains:sodium 1mg
- store at 20-25°C (68-77°F)
- alcohol-free
- dosage cup provided

Inactive ingredients

cherry flavor, citric acid, FD and C red no. 40, glycerin, high fructose corn syrup, sucrose, sucralose, menthol, propylene glycol, purified water, xanthan gum, polysorbate, saccharin sodium, sodium benzoate

Package label

Tussin Chest